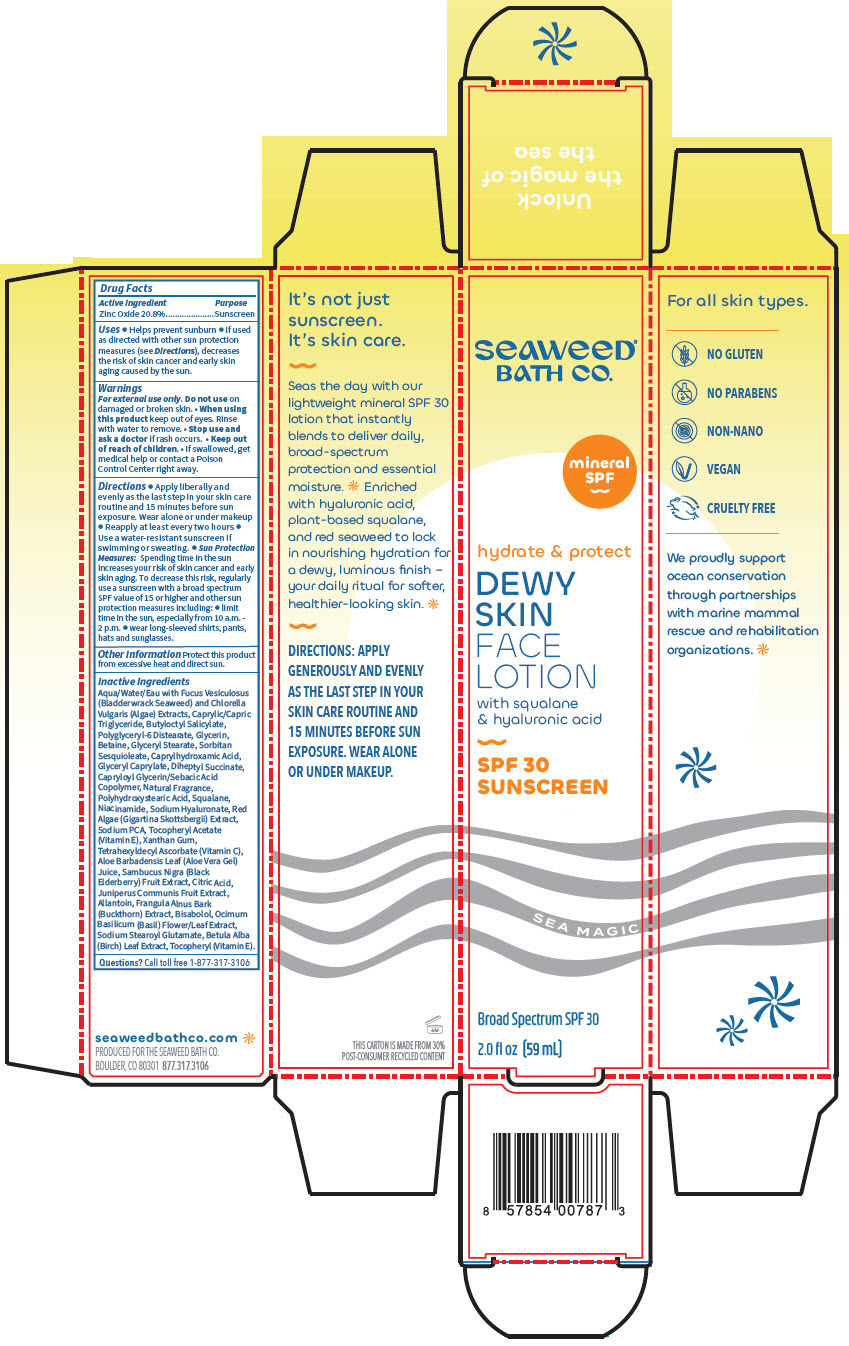 DRUG LABEL: Dewy Skin Face
NDC: 81159-387 | Form: LOTION
Manufacturer: The Seaweed Bath Co.
Category: otc | Type: HUMAN OTC DRUG LABEL
Date: 20230210

ACTIVE INGREDIENTS: Zinc Oxide 20.8 g/100 mL
INACTIVE INGREDIENTS: WATER; FUCUS VESICULOSUS; CHLORELLA VULGARIS; MEDIUM-CHAIN TRIGLYCERIDES; BUTYLOCTYL SALICYLATE; POLYGLYCERYL-6 DISTEARATE; GLYCERIN; BETAINE; GLYCERYL MONOSTEARATE; SORBITAN SESQUIOLEATE; CAPRYLHYDROXAMIC ACID; GLYCERYL MONOCAPRYLATE; DIHEPTYL SUCCINATE; CAPRYLOYL GLYCERIN/SEBACIC ACID COPOLYMER (2000 MPA.S); POLYHYDROXYSTEARIC ACID STEARATE; SQUALANE; NIACINAMIDE; HYALURONATE SODIUM; SODIUM PYRROLIDONE CARBOXYLATE; .ALPHA.-TOCOPHEROL ACETATE; XANTHAN GUM; TETRAHEXYLDECYL ASCORBATE; ALOE VERA LEAF; SAMBUCUS NIGRA FLOWERING TOP; CITRIC ACID MONOHYDRATE; JUNIPER BERRY; ALLANTOIN; FRANGULA ALNUS BARK; LEVOMENOL; BASIL; SODIUM STEAROYL GLUTAMATE; BETULA PUBESCENS LEAF; TOCOPHEROL

Dewy Skin Face Lotion

Drug Facts

Active Ingredient

Zinc Oxide 20.8%

Purpose

Sunscreen

Uses

- Helps prevent sunburn
- if used as directed with other sun protection measures (see Directions), decreases the risk of skin cancer and early skin aging caused by the sun.

Warnings

For external use only.

Do not use on damaged or broken skin.

- When using this product keep out of eyes. Rinse with water to remove.

- Stop use and ask a doctor if rash occurs.

- Keep out of reach of children.
- If swallowed, get medical help or contact a Poison Control Center right away.

Directions

- Apply liberally and evenly as the last step in your skin care routine and 15 minutes before sun exposure. Wear alone or under makeup
- Reapply at least every two hours
- Use a water-resistant sunscreen if swimming or sweating.
- Sun Protection Measures: Spending time in the sun increases your risk of skin cancer and early skin aging. To decrease this risk, regularly use a sunscreen with a broad spectrum SPF value of 15 or higher and other sun protection measures including:
  - limit time in the sun, especially from 10 a.m. - 2 p.m.
  - wear long-sleeved shirts, pants, hats and sunglasses.

Other Information

Protect this product from excessive heat and direct sun.

Inactive Ingredients

Aqua/Water/Eau with Fucus Vesiculosus (Bladderwrack Seaweed) and Chlorella Vulgaris (Algae) Extracts, Caprylic/Capric Triglyceride, Butyloctyl Salicylate, Polyglyceryl-6 Distearate, Glycerin, Betaine, Glyceryl Stearate, Sorbitan Sesquioleate, Caprylhydroxamic Acid, Glyceryl Caprylate, Diheptyl Succinate, Capryloyl Glycerin/Sebacic Acid Copolymer, Natural Fragrance, Polyhydroxystearic Acid, Squalane, Niacinamide, Sodium Hyaluronate, Red Algae (Gigartina Skottsbergii) Extract, Sodium PCA, Tocopheryl Acetate (Vitamin E), Xanthan Gum, Tetrahexyldecyl Ascorbate (Vitamin C), Aloe Barbadensis Leaf (Aloe Vera Gel) Juice, Sambucus Nigra (Black Elderberry) Fruit Extract, Citric Acid, Juniperus Communis Fruit Extract, Allantoin, Frangula Alnus Bark (Buckthorn) Extract, Bisabolol, Ocimum Basilicum (Basil) Flower/Leaf Extract, Sodium Stearoyl Glutamate, Betula Alba (Birch) Leaf Extract, Tocopheryl (Vitamin E).

Questions?

Call toll free 1-877-317-3106

PRINCIPAL DISPLAY PANEL - 59 mL Bottle Carton

SEAWEED®
BATH CO.

mineral
SPF

hydrate & protect

DEWY
SKIN
FACE
LOTION

with squalane
& hyaluronic acid

SPF 30
SUNSCREEN

SEA MAGIC

Broad Spectrum SPF 30

2.0 fl oz (59 mL)